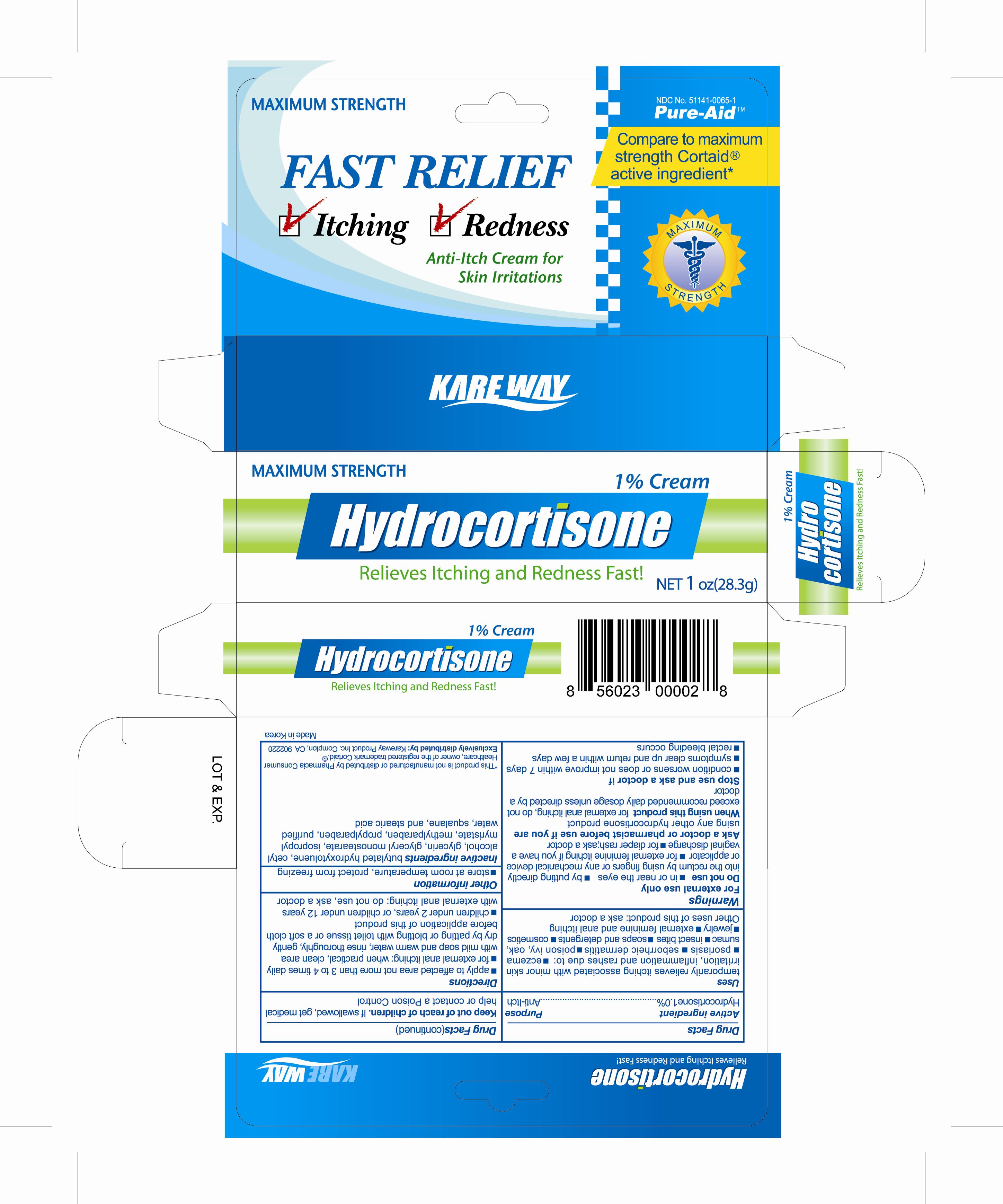 DRUG LABEL: Hydrocortisone
NDC: 51141-0002 | Form: CREAM
Manufacturer: Neopharm Co,. Ltd 
Category: otc | Type: HUMAN OTC DRUG LABEL
Date: 20110110

ACTIVE INGREDIENTS: Hydrocortisone 1 g/100 g
INACTIVE INGREDIENTS: Cetyl alcohol; Glycerin; Squalane

Hydrocortisone 1%

Active Ingredient
Hydrocortisone 1%

Purpose
Anti-itch

Keep out of reach of children
if swallowed, get medical help or contact a Poison Control

Uses
temporarily relieves itching
associated with minor skin irritation, inflammation and rashes due to :

- psoriasis
- seborrheic dermatitis
- poison ivy,oak,sumac
- insect bites

Other uses of this product: ask a doctor

Warnings
For external use only
Do not use
* in or near the eyes
* by putting directly into the rectum by using figers or any mechanical device
or applicator
* for diaper rash; ask a doctor

Directions

- apply to affected area not more than 3 to 4 time daily
- for external anal itching: when practical, clean area with mild soap and warm

Inactive ingredients
Cetyl alcohol, Buthylated hydroxytoluene, Glycerin, Glyceryl monostearate, Isopropyl myristate, Myreistoyl/palmitoyl/oxostearamide/arachamide MEA, Methylparaben, PEG-15 glyceryl stearate, Squalane, Stearic acid, Propylparaben, Purified water
Hydrocortosone